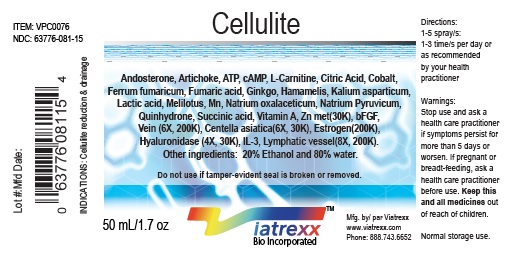 DRUG LABEL: Viatrexx-Cellulite
NDC: 63776-081 | Form: SPRAY
Manufacturer: VIATREXX BIO INCORPORATED
Category: homeopathic | Type: HUMAN OTC DRUG LABEL
Date: 20190319

ACTIVE INGREDIENTS: Androsterone 30 [kp_C]/1 mL; Artichoke 30 [kp_C]/1 mL; Adenosine Triphosphate 30 [kp_C]/1 mL; Basic Fibroblast Growth Factor (Human) 200 [kp_C]/1 mL; Ersofermin 200 [kp_C]/1 mL; Adenosine Cyclic Phosphate 30 [kp_C]/1 mL; Levocarnitine 30 [kp_C]/1 mL; Centella Asiatica 30 [kp_C]/1 mL; Citric Acid Monohydrate 30 [kp_C]/1 mL; Cobalt 30 [kp_C]/1 mL; Estrogens, Esterified 200 [kp_C]/1 mL; Ferrous Fumarate 30 [kp_C]/1 mL; Fumaric Acid 30 [kp_C]/1 mL; Heptaminol 30 [kp_C]/1 mL; Hamamelis Virginiana Bark 30 [kp_C]/1 mL; Hyaluronidase 30 [kp_C]/1 mL; Interleukin-3 200 [kp_C]/1 mL; Potassium Aspartate 30 [kp_C]/1 mL; Lactic Acid 30 [kp_C]/1 mL; Bos Taurus Lymph Vessel 200 [kp_C]/1 mL; Sus Scrofa Lymph Vessel 200 [kp_C]/1 mL; Melilotus Officinalis Whole 30 [kp_C]/1 mL; Manganese 30 [kp_C]/1 mL; Sodium Diethyl Oxalacetate 30 [kp_C]/1 mL; Sodium Pyruvate 30 [kp_C]/1 mL; Quinhydrone 30 [kp_C]/1 mL; Succinic Acid 30 [kp_C]/1 mL; Bos Taurus Vein 200 [kp_C]/1 mL; Sus Scrofa Vein 200 [kp_C]/1 mL; Vitamin A 30 [kp_C]/1 mL; Zinc 30 [kp_C]/1 mL
INACTIVE INGREDIENTS: Alcohol; Water

Cellulite

Active Ingredients

Androsterone (30K), Artichoke (30K), ATP (30K), bFGF (6X, 200K), cAMP (30K), L-Carnitine (30K), Centella asiatica (6X, 30K), Citric Acid (30K), Cobalt (30K), Estrogen (200K), Ferrum fumaricum (30K), Fumaric acid (30K), Ginkgo (30K), Hamamelis (30K), Hyaluronidase (4X, 30K), IL-3 (8X, 200K), Kalium asparticum (30K), Lactic acid (30K), Lymphatic vessel (8X, 200K), Melilotus (30K), Mn (30K), Natrum oxalaceticum (30K), Natrum pyruvicum (30K), Quinhydrone (30K), Succinic acid (30K), Vein (6X, 200K), Vitamin A (30K), Zinc (30K).

Purpose

Androsterone
Artichoke
ATP
bFGF
cAMP
L-Carnitine
Centella asiatica
Citric Acid
Cobalt
Estrogen
Ferrum fumaricum
Fumaric acid
Ginkgo
Hamamelis
Hyaluronidase
IL-3
Kalium asparticum
Lactic acid
Lymphatic vessel
Melilotus
Mn
Natrum oxalaceticum
Natrum pyruvicum
Quinhydrone
Succinic acid
Vein
Vitamin A
Zinc

Hormonal support
Cholesterol balance
Cell respiration
Regeneration
Intra-Cellular support
Metabolic support
Adaptogen
Cell respiration
GI function
Hormonal support
Cell respiration
Cell respiration
Circulation support
Venous support
Regeneration
Immune support
Cell respiration
Cell respiration
Lymphatic support
Drainage
Drainage
Cell respiration
Cell respiration
Krebs cycle support
Cell respiration
Regeneration
Metabolism
Metabolism

Uses

Cellulite drainage & tonification, metabolism and lipid balance, hormonal support, circulatory support and regeneration.

Warnings

Stop use and ask a health care practitioner if symptoms persist for more than 5 days or worsen. If pregnant or breastfeeding, ask a health care practitioner before use.

Dosage

1-5 spray(s); 1-3 time(s) per day or as recommended by your health care practitioner.

Product Availability

Product may be acquired in 0.5, 30 ,50, 100, 250, 500, 1,000 mL bottles.

Inactive Ingredients

20% Alcohol and 80% Water.

Other Information

Normal storage use.
Do not use if tamper-evident seal is broken or removed.

References upon request

To report SUSPECTED ADVERSE REACTIONS, contact the FDA at 1-800-FDA-1088 or www.fda.gov/medwatch
Distributed by Viatrexx Bio Incorporated
Newark, DE, USA, 19713
Manufactured by
8046255 Canada Inc
Beloeil, Qc, J3G 6S3
Date of last revision March 2019
For questions and comments
Info@Viatrexx.com
www.Viatrexx.com

PACKAGE LABEL.PRINCIPAL DISPLAY PANEL

NDC: 63776-081-11
Item: VPC0076
Viatrexx Bio Incorporated
Viatrexx-Cellulite
0.5 mL ampule
For Oral and Topical Use
Expiry date: Lot #:
Manufactured for:
Viatrexx Bio Incorporated Newark, DE, USA, 19713
www.Viatrexx.com
Ingredients, homeopathic
See insert or www.viatrexx.com
Inactives: Alcohol 20%, Water 80%

NDC: 63776-081-14
Item: VPC0076
Viatrexx Bio Incorporated
Viatrexx-Cellulite 30 mL spray bottle
For Oral and Topical Use
Expiry date: Lot #:
Manufactured for:
Viatrexx Bio Incorporated Newark, DE, USA, 19713
www.Viatrexx.com
Ingredients, homeopathic
See insert or www.viatrexx.com
Inactives: Alcohol 20%, Water 80%

NDC: 63776-081-15
Item: VPC0076
Viatrexx Bio Incorporated
Viatrexx-Cellulite
50 mL spray bottle
For Oral and Topical Use
Expiry date: Lot #:
Manufactured for:
Viatrexx Bio Incorporated Newark, DE, USA, 19713
www.Viatrexx.com
Ingredients, homeopathic
See insert or www.viatrexx.com
Inactives: Alcohol 20%, Water 80%

NDC: 63776-081-16
Item: VPC0076
Viatrexx Bio Incorporated
Viatrexx-Cellulite
100 mL bottle
For Oral and Topical Use
Expiry date: Lot #:
Manufactured for:
Viatrexx Bio Incorporated Newark, DE, USA, 19713
www.Viatrexx.com
Ingredients, homeopathic
See insert or www.viatrexx.com
Inactives: Alcohol 20%, Water 80%

NDC: 63776-081-17
Item: VPC0076
Viatrexx Bio Incorporated
Viatrexx-Cellulite
250 mL bottle
For Oral and Topical Use
Expiry date: Lot #:
Manufactured for:
Viatrexx Bio Incorporated Newark, DE, USA, 19713
www.Viatrexx.com
Ingredients, homeopathic
See insert or www.viatrexx.com
Inactives: Alcohol 20%, Water 80%